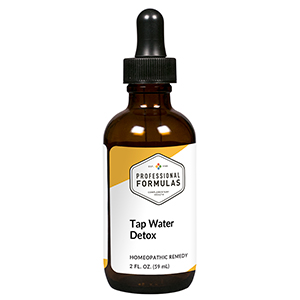 DRUG LABEL: Tap Water Detox
NDC: 63083-6018 | Form: LIQUID
Manufacturer: Professional Complementary Health Formulas
Category: homeopathic | Type: HUMAN OTC DRUG LABEL
Date: 20190815

ACTIVE INGREDIENTS: 2,3,7,8-TETRACHLORODIBENZO-P-DIOXIN 60 [hp_X]/59 mL; BROMINE 30 [hp_X]/59 mL; CHLORINE 30 [hp_X]/59 mL; CHLOROFORM 30 [hp_X]/59 mL; COPPER 30 [hp_X]/59 mL; FLUORIDE ION 30 [hp_X]/59 mL; IRON 30 [hp_X]/59 mL; LEAD 30 [hp_X]/59 mL; SODIUM FLUORIDE 30 [hp_X]/59 mL; PHENOL 30 [hp_X]/59 mL; PENTAERYTHRITOL TETRAKIS(3-(3,5-DI-TERT-BUTYL-4-HYDROXYPHENYL)PROPIONATE) 30 [hp_X]/59 mL; FENSON 30 [hp_X]/59 mL
INACTIVE INGREDIENTS: ALCOHOL; WATER

X18

ACTIVE INGREDIENTS

Dioxin 60X
and all the following at 30X, 60X:
Bromium
Chlorinum
Chloroformum
Copper
Fluoride
Iron
Lead
Natrum fluoratum
Phenol
Plastics
Polychlorinated biphenyls (PCBs)

QUESTIONS

Professional Formulas

PO Box 2034 Lake Oswego, OR 97035

INDICATIONS

For the temporary relief of mild abdominal pain, nausea or vomiting, shortness of breath, minor rash or itchy skin, or occasional headache due to sensitivity to or exposure to common tap water additives or contaminants.*

PURPOSE

*Claims based on traditional homeopathic practice, not accepted medical evidence. Not FDA evaluated.

WARNINGS

Consult a doctor if condition worsens or symptoms persist. Keep out of the reach of children. In case of overdose, get medical help or contact a poison control center right away. If pregnant or breastfeeding, ask a healthcare professional before use.

Keep out of the reach of children.

PREGNANCY OR BREAST FEEDING

If pregnant or breastfeeding, ask a healthcare professional before use.

DIRECTIONS

Place drops under tongue 30 minutes before/after meals. Adults and children 12 years and over: Take 10 drops up to 3 times per day. Consult a physician for use in children under 12 years of age.

OTHER INFORMATION

Tamper resistant. If seal is broken, do not use. After opening, close container tightly and store at room temperature away from heat.

INACTIVE INGREDIENTS

20% ethanol, purified water.

LABEL

Est 1985

Professional Formulas

Complementary Health

Tap Water Detox

Homeopathic Remedy

2 FL. OZ. (59 mL)